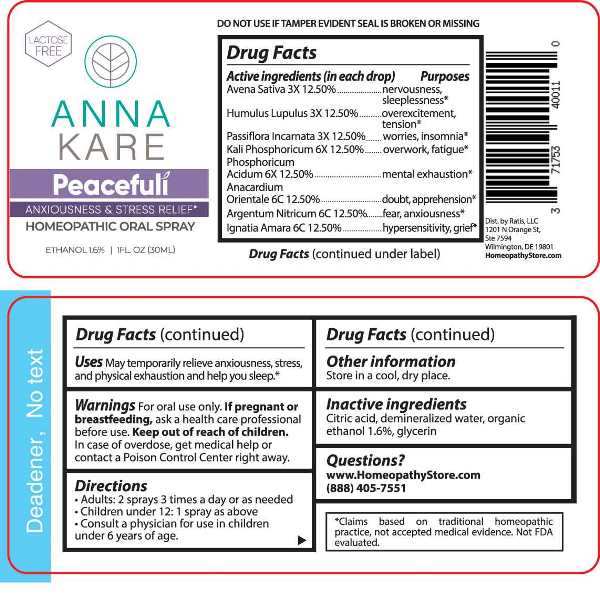 DRUG LABEL: Peacefuli
NDC: 71753-4001 | Form: SPRAY
Manufacturer: Ratis, LLC
Category: homeopathic | Type: HUMAN OTC DRUG LABEL
Date: 20230525

ACTIVE INGREDIENTS: AVENA SATIVA FLOWERING TOP 3 [hp_X]/1 mL; HOPS 3 [hp_X]/1 mL; PASSIFLORA INCARNATA FLOWERING TOP 3 [hp_X]/1 mL; DIBASIC POTASSIUM PHOSPHATE 6 [hp_X]/1 mL; PHOSPHORIC ACID 6 [hp_X]/1 mL; SEMECARPUS ANACARDIUM JUICE 6 [hp_C]/1 mL; SILVER NITRATE 6 [hp_C]/1 mL; STRYCHNOS IGNATII SEED 6 [hp_C]/1 mL
INACTIVE INGREDIENTS: WATER; ALCOHOL; GLYCERIN; CITRIC ACID MONOHYDRATE

DRUG FACTS:

ACTIVE INGREDIENT:

(in each drop) Avena Sativa 3X 12.50%, Humulus Lupulus 3X 12.50%, Passiflora Incarnata 3X 12.50%, Kali Phosphoricum 6X 12.50%, Phosphoricum Acidum 6X 12.50%, Anacardium Orientale 6C 12.50%, Argentum Nitricum 6C 12.50%, Ignatia Amara 6C 12.50%.

PURPOSE:

Avena Sativa – nervousness, sleeplessness,* Humulus Lupulus – overexcitement, tension,* Passiflora Incarnata – worries, insomnia,* Kali Phosphoricum – overwork, fatigue,* Phosphoricum Acidum – mental exhaustion,* Anacardium Orientale – doubt, apprehension, * Argentum Nitricum – fear, anxiousness,* Ignatia Amara – hypersensitivity, grief.*

USES:

May temporarily relieve anxiousness, stress, and physical exhaustion and help you sleep.*

*Claims based on traditional homeopathic practice, not accepted medial evidence. Not FDA evaluated.

WARNINGS:

For oral use only.

If pregnant or breast-feeding, ask a health care professional before use.

Keep out of reach of children. In case of overdose, get medical help or contact a Poison Control Center right away.

DO NOT USE IF TAMPER EVIDENT SEAL IS BROKEN OR MISSING

KEEP OUT OF REACH OF CHILDREN:

In case of overdose, get medical help or contact a Poison Control Center right away.

DIRECTIONS:

• Adults: 2 sprays 3 times a day or as needed.

• Children under 12: 1 spray as above

• Consult a physician for use in children under 6 years of age.

Store in a cool, dry place.

INACTIVE INGREDIENTS:

Citric acid, demineralized water, organic ethanol 1.6%, glycerin

QUESTIONS:

Dist. by Ratis, LLC:

1201 N Orange St,

Ste 7594

Wilmington, DE 19801

www.HomeopathyStore.com

(888) 405-7551

PACKAGE LABEL DISPLAY:

LACTOSE FREE

ANNA

KARE

Peacefuli

ANXIETY & STRESS RELIEF*

HOMEOPATHIC ORAL SPRAY

1 FL. OZ (30ML)